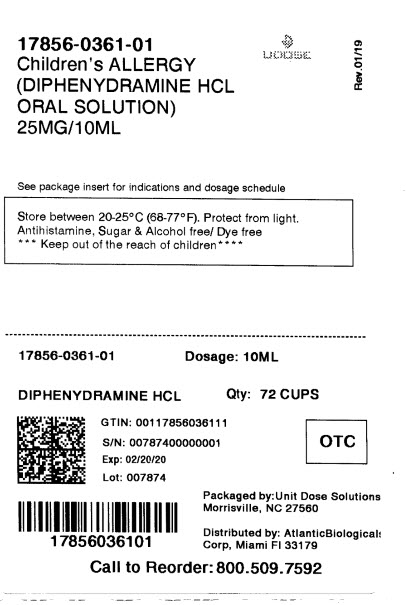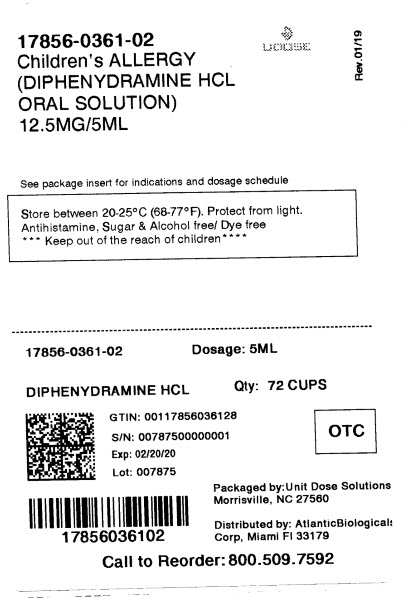 DRUG LABEL: Childrens Allergy
NDC: 17856-0361 | Form: SOLUTION
Manufacturer: ATLANTIC BIOLOGICALS CORP.
Category: otc | Type: Human OTC Drug Label
Date: 20210120

ACTIVE INGREDIENTS: DIPHENHYDRAMINE HYDROCHLORIDE 12.5 mg/5 mL
INACTIVE INGREDIENTS: ANHYDROUS CITRIC ACID; CARBOXYMETHYLCELLULOSE SODIUM; GLYCERIN; WATER; SACCHARIN SODIUM; SODIUM BENZOATE; SODIUM CITRATE; SORBITOL

Drug Facts

Active ingredient [in each 5 mL]
Diphenhydramine HCl, USP 12.5 mg

Purpose

Antihistamine

Uses

- temporarily relieves these symptoms due to hay fever or other upper respiratory allergies:
- runny nose
- sneezing
- itchy, watery eyes
- itching of the nose or throat

Warnings

Do not use

- to make a child sleepy
- with any other product containing diphenhydramine, even one used on skin

Ask a doctor before use if the child has

- glaucoma
- a breathing problem such as emphysema or chronic bronchitis
- a sodium-restricted diet

Ask a doctor or pharmacist before use if you

are taking sedatives or tranquilizers

When using this product

- sedatives and tranquilizers may increase drowsiness
- marked drowsiness may occur
- excitability may occur, especially in children

Keep out of reach of children.

In case of overdose, get medical help or contact a Poison Control Center right away. (1-800-222-1222)

Directions

- take every 4 to 6 hours, or as directed by a doctor
- do not take more than 6 doses in 24 hours
- mL = milliliter

Age (yr) | Dose (mL)
children under 6 years of age | ask a doctor
children 6 years to under 12 years of age | 5 mL to 10 mL

Attention: Use only enclosed dosing cup specifically designed for use with this product. Do not use any other dosing device.

Other information

- each 5 mL contains: sodium 9 mg
- store between 20-25°C (68-77°F). Protect from light. Store in outer carton until contents used
- see bottom panel for lot number and expiration date

Inactive ingredients

anhydrous citric acid, carboxymethyl cellulose sodium, flavor, glycerin, purified water, saccharin sodium, sodium benzoate, sodium citrate, sorbitol solution

Questions or comments? 1-855-274-4122

Distributed ByATLANTIC BIOLOGICALS CORP.

20101 N.E 16TH PLACE

MIAMI, FL 33179

PACKAGE LABEL-PRINCIPAL DISPLAY PANEL

NDC 17856-0361-01
Compare to
Children's Benadryl®
active ingredient*
Children's
ALLERGY
Antihistamine
diphenhydramine hydrochloride
25mg/10 mL oral solution
liquid medication

Relieves:

- Runny Nose
- Sneezing
- Itchy, Watery Eyes
- Itchy Throat

Sugar & Alcohol Free
Dye-FreeBubble Gum Flavored
NDC 17856-0361-02

Compare to
Children's Benadryl®
active ingredient*

Children's
ALLERGY

Antihistamine

diphenhydramine hydrochloride
12.5mg/5mL oral solution
liquid medication

Relieves:

Runny Nose
Sneezing
Itchy, Watery Eyes
Itchy Throat
Sugar & Alcohol Free

Dye-Free
Bubble Gum Flavored